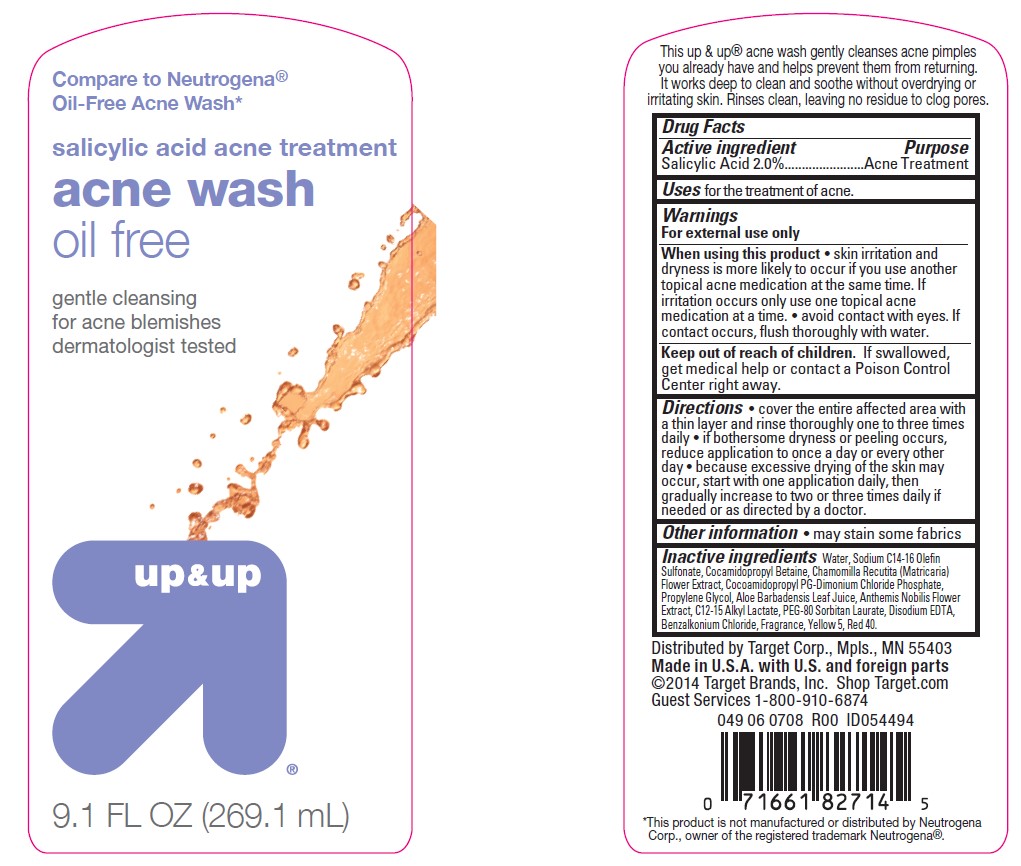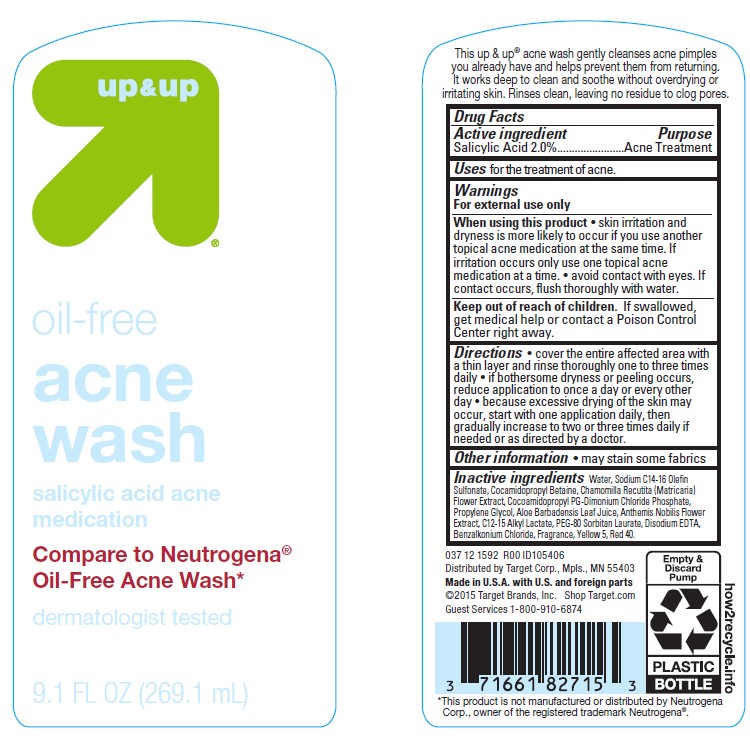 DRUG LABEL: Up and Up
NDC: 11673-024 | Form: LIQUID
Manufacturer: TARGET CORPORATION
Category: otc | Type: HUMAN OTC DRUG LABEL
Date: 20241014

ACTIVE INGREDIENTS: SALICYLIC ACID 20 mg/1 mL
INACTIVE INGREDIENTS: WATER; FD&C YELLOW NO. 5; SODIUM C14-16 OLEFIN SULFONATE; COCAMIDOPROPYL PG-DIMONIUM CHLORIDE PHOSPHATE; PEG-80 SORBITAN LAURATE; C12-15 ALKYL LACTATE; CHAMAEMELUM NOBILE FLOWER; EDETATE DISODIUM; COCAMIDOPROPYL BETAINE; PROPYLENE GLYCOL; BENZALKONIUM CHLORIDE; ALOE VERA LEAF; CHAMOMILE; FD&C RED NO. 40; ALCOHOL

Up & Up Oil-Free Acne Wash

Active ingredient

Salicylic Acid 2.0%

Purpose

Acne Treatment

Uses

for the treatment of acne.

Warnings

For external use only

When using this product

• skin irritation and dryness is more likely to occur if you use another topical acne medication at the same time. If irritation occurs only use one topical acne medication at a time. • avoid contact with eyes. If contact occurs, flush thoroughly with water.

Keep out of reach of children.

If swallowed, get medical help or contact a Poison Control Center right away.

Directions

• cover the entire affected area with a thin layer and rinse thoroughly one to three times daily • if bothersome dryness or peeling occurs, reduce application to once a day or every other day • because excessive drying of the skin may occur, start with one application daily, then gradually increase to two or three times daily if needed or as directed by a doctor.

Other information

• may stain some fabric

Inactive ingredients

Water, Sodium C14-16 Olefin Sulfonate, Cocamidopropyl Betaine, Chamomilla Recutita (Matricaria) Flower Extract, Cocamidopropyl PG-Dimonium Chloride Phosphate, Propylene Glycol, Aloe Babadensis Leaf Juice, Anthemis Nobilis Flower Extract, C12-C15 Alkyl Lactate, PEG-80 Sorbitan Laurate, Disodium EDTA, Benzalkonium Chloride, Fragrance, Yellow 5, Red 40.